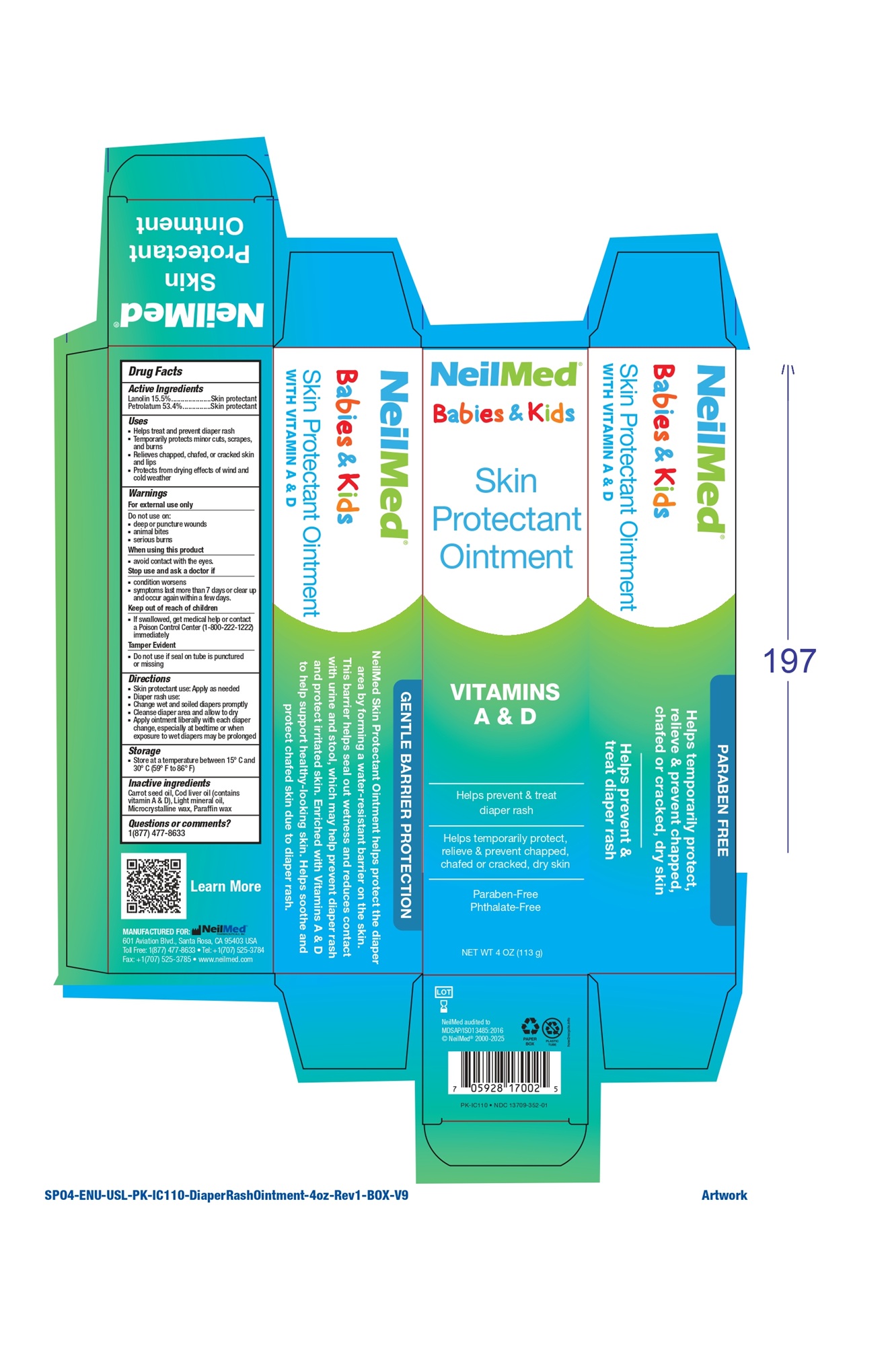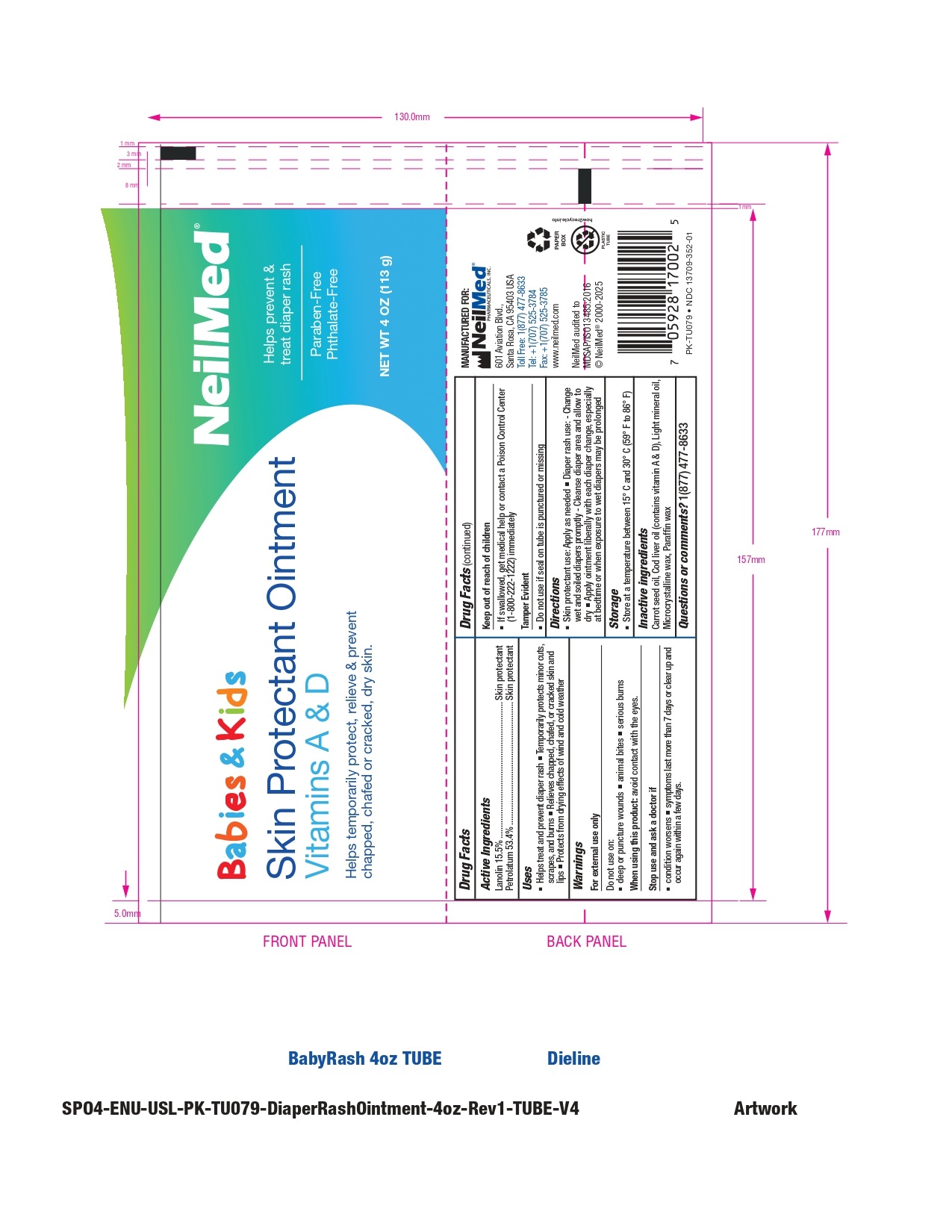 DRUG LABEL: Skin Protectant for Babies and kids
NDC: 13709-352 | Form: OINTMENT
Manufacturer: Neilmed Pharmaceuticals Inc.
Category: otc | Type: HUMAN OTC DRUG LABEL
Date: 20260102

ACTIVE INGREDIENTS: LANOLIN 155 mg/1 g; PETROLATUM 534 mg/1 g
INACTIVE INGREDIENTS: MICROCRYSTALLINE WAX; PARAFFIN; LIGHT MINERAL OIL; CARROT SEED OIL; COD LIVER OIL

Skin Protectant

Drug Facts: Active Ingredients

Lanolin 15.5%

Petrolatum 53.4%

Purpose

Lanolin - Skin protectant

Petrolatum - Skin protectant

Uses

- Helps treat and prevent diaper rash
- Temporarily protects minor cuts, scrapes, and burns
- Relieves chapped, chafed, or cracked skin and lips
- Protects from drying effects of wind and cold weather

Warnings

For external use only

Do not use on

- deep or puncture wounds
- animal bites
- serious burns

When using this product

- avoid contact with the eyes.

Stop use and ask a doctor if

- condition worsens
- symptoms last more than 7 days or clear up and occur again within a few days.

Keep out of reach of children

- If swallowed, get medical help or contact a Poison Control Center (1-800-222-1222) immediately.

Directions

- Skin protectant use: apply as needed
- Diaper rash use:
- Change wet and soiled diapers promptly
- Cleanse the diaper area, and allow to dry
- Apply ointment liberally with each diaper change, especially at bedtime or anytime when exposure to wet diapers may be prolonged

Storage

- Do not exceed 30°C (86°F)

Inactive Ingredients

Carrot seed oil

Cod liver oil(contains vitamin A & D)

Light mineral oil

Microcrystalline wax

Paraffin wax

Tamper Evident

- Do not use if seal on tube is punctured or missing.